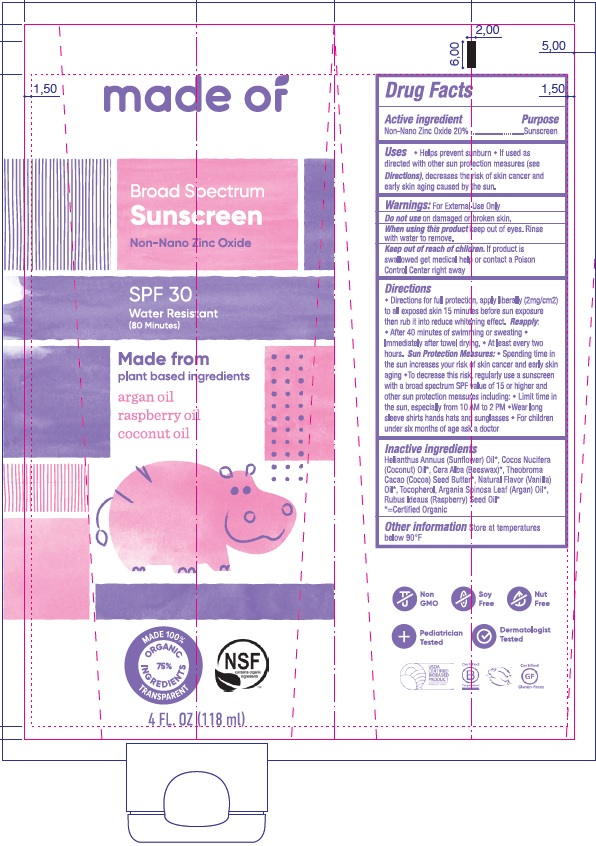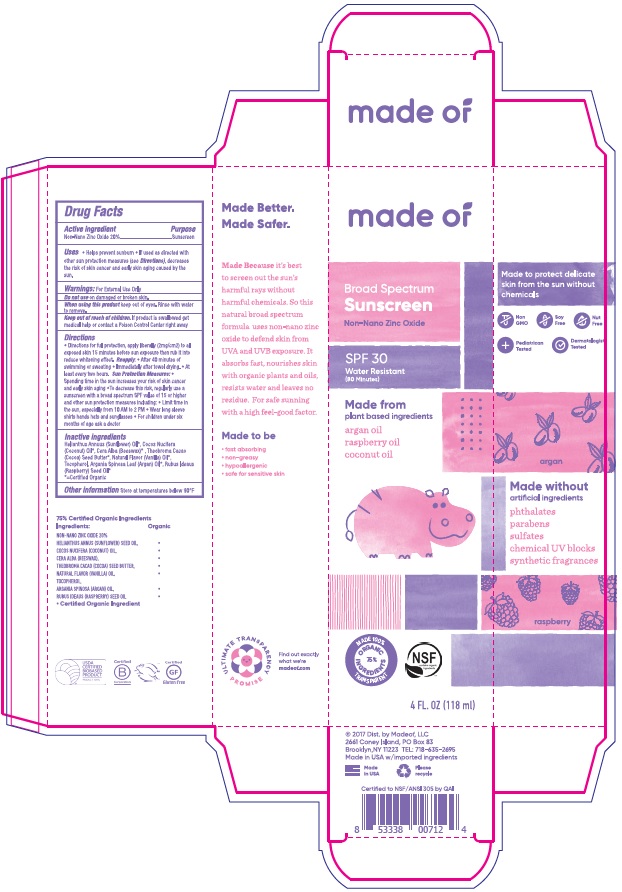 DRUG LABEL: SUNSCREEN
NDC: 62932-182 | Form: OINTMENT
Manufacturer: Private Label Select Ltd CO
Category: otc | Type: HUMAN OTC DRUG LABEL
Date: 20220104

ACTIVE INGREDIENTS: ZINC OXIDE 20 g/100 g
INACTIVE INGREDIENTS: HELIANTHUS ANNUUS SEED WAX; COCONUT OIL; YELLOW WAX; THEOBROMA GRANDIFLORUM SEED BUTTER; VANILLA; TOCOPHEROL; ARGAN OIL; RASPBERRY SEED OIL

made of Sunscreen SPF30